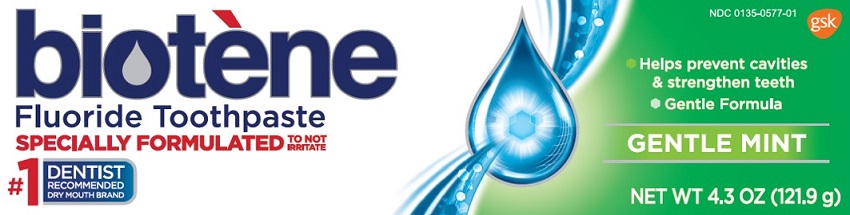 DRUG LABEL: biotene
NDC: 0135-0577 | Form: PASTE
Manufacturer: Haleon US Holdings LLC
Category: otc | Type: HUMAN OTC DRUG LABEL
Date: 20241104

ACTIVE INGREDIENTS: SODIUM MONOFLUOROPHOSPHATE 1.4 mg/1 g
INACTIVE INGREDIENTS: SORBITOL; GLYCERIN; CALCIUM PYROPHOSPHATE; WATER; HYDRATED SILICA; XYLITOL; SILICON DIOXIDE; HYDROXYETHYL CELLULOSE, UNSPECIFIED; ISOCETETH-20; XANTHAN GUM; SODIUM BENZOATE; CALCIUM LACTATE ANHYDROUS

Drug Facts

Active ingredient

Sodium monofluorophosphate 0.76% (0.14% w/v fluoride ion)

Purpose

Anticavity

Use

aids in the prevention of dental cavities.

Warnings

When using this product,

if irritation occurs discontinue use.

Keep out of reach of children under 6 years of age.

If more than used for bushing is accidentally swallowed, get medical help or contact a Poison Control Center right away.

Directions

- adults and children 2 years of age and older:
  - apply toothpaste onto a toothbrush
  - brush teeth thoroughly, preferable after each meal or at least twice a day, and not more than 3 times a day, or as directed by a dentist or doctor. Minimizing swallowing. Spit out after brushing.
  - to minimize swallowing for children under 6 years of age, use a pea-sized amoun and supervise brushing and rinsing until good habits are established.
- children under 2 years of age: Consult a dentist or doctor.

Other information

store at or below 25ºC (77ºF)

Inactive ingredients

sorbitol, glycerin, calcium pyrophosphate, water, hydrated silica, xylitol, silica, hydroxyethyl cellulose, isoceteth-20, cellulose gum, flavor, sodium benzoate, sodium lactate.

Questions or comments?

Call toll-free 1-800-922-5856

Additional information

This product contains no Sodium Lauryl Sulfate (SLS)

Trademarks are owned by or licensed to the GSK group of companies.

Distributed by:

GSK Consumer Healthcare

Warren, NJ 07059

@2019 GSK group of companies or its licensor.

Questions or Comments?

1-800-922-5856

Principal Display Panel

NDC 0135-0577-01

biotene®

Fluoride Toothpaste

SPECIALLY FORMULATED TO NOT IRRITATE

Helps prevent cavities & strengthen teeth

Gentle Formula

GENTLE MINT

NET WT 4.3 OZ (121.9g)

1000114 Front Carton